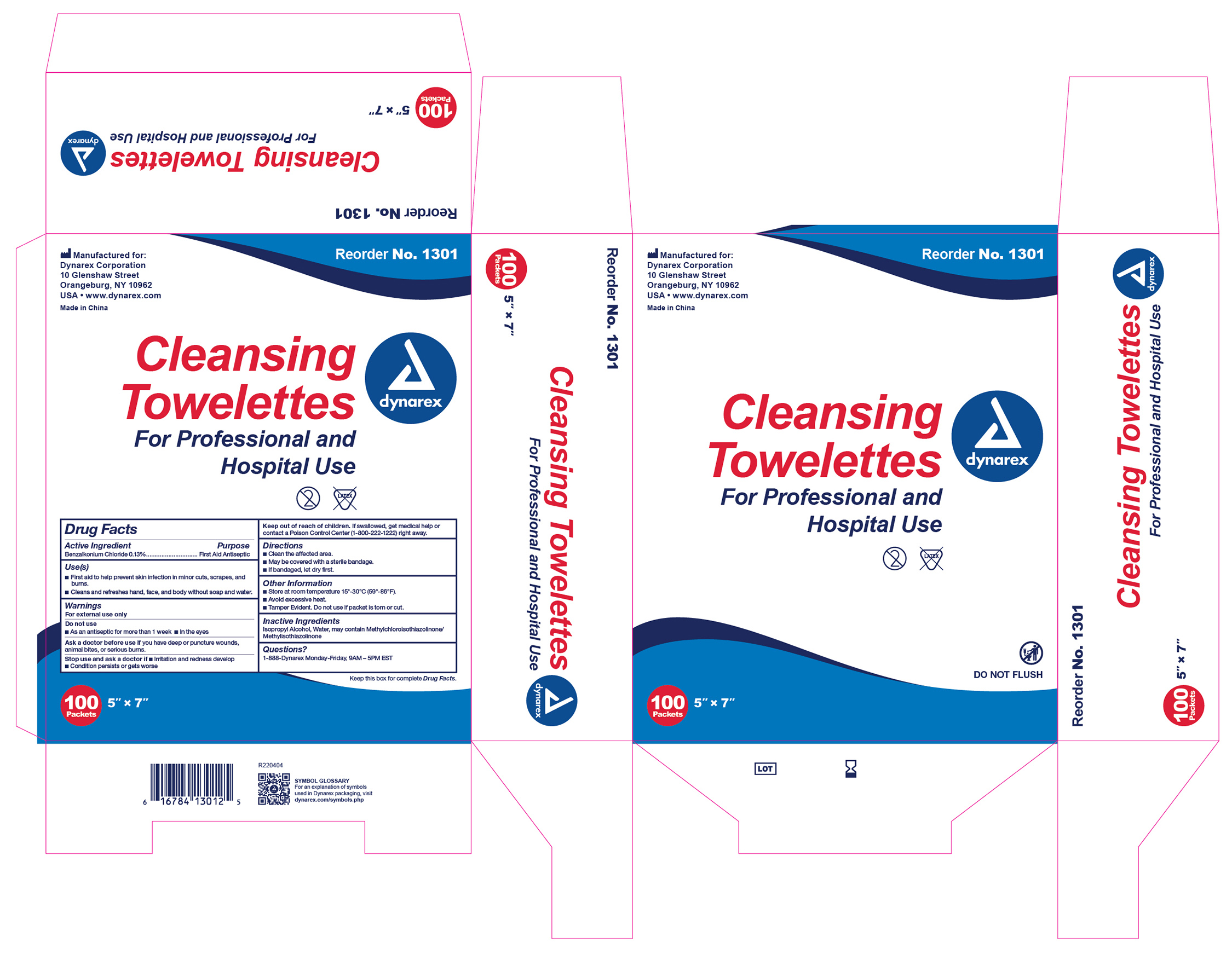 DRUG LABEL: BZK Pads
NDC: 67777-243 | Form: SWAB
Manufacturer: Dynarex Corporation
Category: otc | Type: HUMAN OTC DRUG LABEL
Date: 20260123

ACTIVE INGREDIENTS: BENZALKONIUM CHLORIDE 1.3 mg/1 mL
INACTIVE INGREDIENTS: WATER; METHYLCHLOROISOTHIAZOLINONE/METHYLISOTHIAZOLINONE MIXTURE; ISOPROPYL ALCOHOL

1301 Cleansing Towelettes NDC 67777-243-01

Active Ingredient

Benzalkonium Chloride 0.13% v/v

Purpose

First Aid Antiseptic

Uses

• First aid to help prevent skin infection in minor cuts, scrapes, and burns.

• Cleans and refreshes hand, face, and body without soap and water.

Warnings

For external use only

Do not use

• As an antiseptic for more than 1 week

• In the eyes

Ask a doctor before use if

you have deep or puncture wounds, animal bites, or serious burns.

Stop use and ask a doctor if

• Irritation and redness develop

• Condition persists or gets worse

Keep out of reach of children

If swallowed, get medical help or contact a Poison Control Center (1-800-222-1222) right away.

Direction

• Clean the affected area.

• May be covered with a sterile bandage

• If bandaged, let dry first

Other Information

• Store at room temperature 15º-30ºC (59º-86ºF).

• Avoid excessive heat.

• Tamper evident. Do not use if packet is torn or cut.

Inactive ingredients

Isopropyl Alcohol, Water, may contain Methylchloroisothiazolinone/Methylisothiazolinone

Questions?

1-888-Dynarex Monday - Friday, 9AM - 5PM EST

Label

1301 Cleansing Towelettes